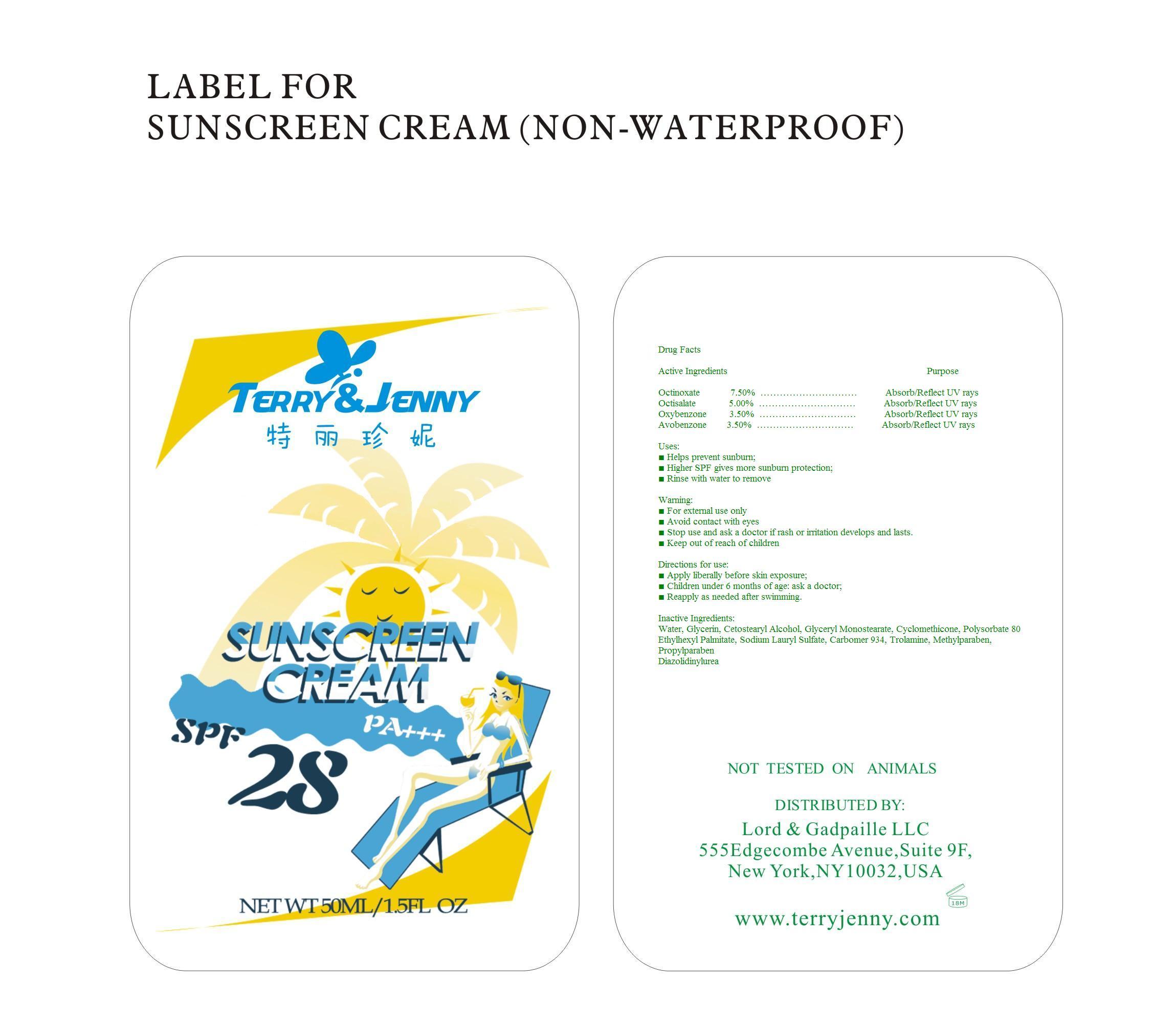 DRUG LABEL: Correway Sunscreen (Non-waterproof)
NDC: 50600-002 | Form: CREAM
Manufacturer: Ningbo Correway Cosmetics Co., Ltd.
Category: otc | Type: HUMAN OTC DRUG LABEL
Date: 20100308

ACTIVE INGREDIENTS: Octinoxate 75 mg/1 g; Octisalate 50 mg/1 g; Oxybenzone 35 mg/1 g; Avobenzone 35 mg/1 g
INACTIVE INGREDIENTS: Water; Glycerin; Cetostearyl Alcohol; Glyceryl Monostearate; Cyclomethicone; Polysorbate 80; Ethylhexyl Palmitate; Sodium Lauryl Sulfate; Carbomer 934; Trolamine; Methylparaben; Propylparaben; Diazolidinylurea

Drug Facts

ACTIVE INGREDIENT

Octinoxate; Octisalate; Oxybenzone; Avobenzone

Stop use and ask a doctor if rash or irritation develops and lasts.
Children under 6 months of age: ask a doctor;

DO NOT USE

Avoid contact with eyes;
Stop use and ask a doctor if rash or irritation develops and lasts.

Keep out of reach of children

PURPOSE

Helps prevent sunburn;
Higher SPF gives more sunburn protection;
Rinse with water to remove;

WHEN USING

Apply liberally before skin exposure;
Reapply as needed after swimming.

Stop use and ask a doctor if rash or irritation develops and lasts.